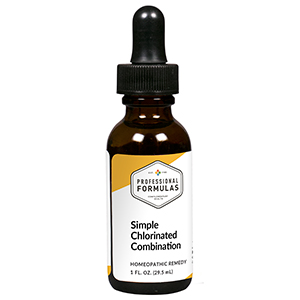 DRUG LABEL: Simple Chlorinated Combination
NDC: 63083-9315 | Form: LIQUID
Manufacturer: Professional Complementary Health Formulas
Category: homeopathic | Type: HUMAN OTC DRUG LABEL
Date: 20190815

ACTIVE INGREDIENTS: BLACK COHOSH 3 [hp_X]/29.5 mL; GELSEMIUM SEMPERVIRENS ROOT 3 [hp_X]/29.5 mL; STRYCHNOS NUX-VOMICA SEED 6 [hp_X]/29.5 mL; BERBERIS VULGARIS ROOT BARK 10 [hp_X]/29.5 mL; CHELIDONIUM MAJUS WHOLE 10 [hp_X]/29.5 mL; CARBON TETRACHLORIDE 12 [hp_X]/29.5 mL; CHLORINE 12 [hp_X]/29.5 mL; CHLOROFORM 12 [hp_X]/29.5 mL; ETHYLENE 12 [hp_X]/29.5 mL; BIS(2,4-DICHLOROBENZOYL) PEROXIDE 14 [hp_X]/29.5 mL; HEXACHLOROPHENE 14 [hp_X]/29.5 mL; TRICHLOROETHYLENE 14 [hp_X]/29.5 mL
INACTIVE INGREDIENTS: ALCOHOL; WATER

R315

ACTIVE INGREDIENTS

Cimicifuga racemosa 3X
Gelsemium sempervirens 3X
Nux vomica 6X
Berberis vulgaris 10X
Chelidonium majus 10X
Carboneum chloratum 12X
Chlorinum 12X
Chloroformum 12X
Ethylene perchlorate 12X
Dichlorobenzol 14X
Hexachlorophene 14X
Trichloroethylene 14X

QUESTIONS

Professional Formulas

PO Box 2034 Lake Oswego, OR 97035

INDICATIONS

For the temporary relief of cough, sneezing, runny nose, occasional headache, nausea, or weakness.*

PURPOSE

*Claims based on traditional homeopathic practice, not accepted medical evidence. Not FDA evaluated.

WARNINGS

Consult a doctor if condition worsens or if symptoms persist. Keep out of the reach of children. In case of overdose, get medical help or contact a poison control center right away. If pregnant or breastfeeding, ask a healthcare professional before use.

Keep out of the reach of children.

PREGNANCY OR BREAST FEEDING

If pregnant or breastfeeding, ask a healthcare professional before use.

DIRECTIONS

Place drops under tongue 30 minutes before/after meals. Adults and children 12 years and over: Take 10 drops up to 3 times per day. Consult a physician for use in children under 12 years of age.

OTHER INFORMATION

Tamper resistant. If seal is broken, do not use. After opening, close container tightly and store at room temperature away from heat.

INACTIVE INGREDIENTS

40% ethanol, purified water.

LABEL

Est 1985

Professional Formulas

Complementary Health

Simple Chlorinated Combination

Homeopathic Remedy

1 FL. OZ. (29.5 mL)